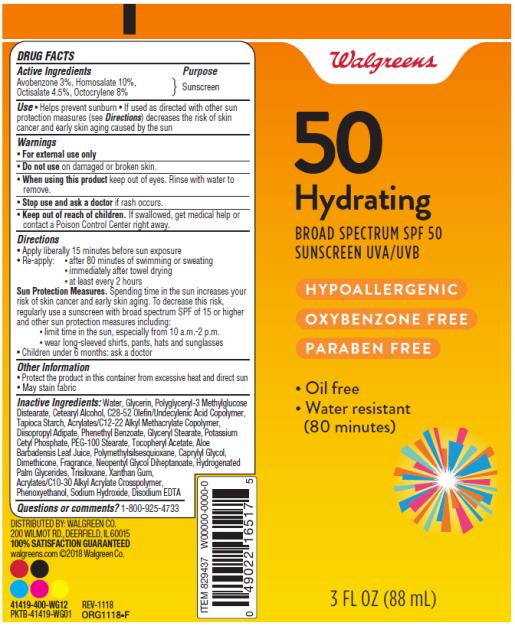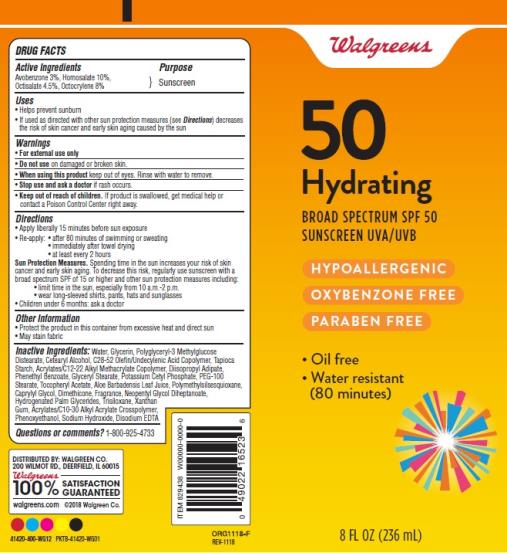 DRUG LABEL: WALG SUN MOISTURIZING SPF 50
NDC: 0363-8223 | Form: LOTION
Manufacturer: Walgreen Company
Category: otc | Type: HUMAN OTC DRUG LABEL
Date: 20181212

ACTIVE INGREDIENTS: AVOBENZONE 3 g/100 mL; HOMOSALATE 10 g/100 mL; OCTISALATE 4.5 g/100 mL; OCTOCRYLENE 8 g/100 mL
INACTIVE INGREDIENTS: ALPHA-TOCOPHEROL ACETATE; WATER; GLYCERIN; CETOSTEARYL ALCOHOL; STARCH, TAPIOCA; DIISOPROPYL ADIPATE; PHENETHYL BENZOATE; GLYCERYL MONOSTEARATE; POTASSIUM CETYL PHOSPHATE; PEG-100 STEARATE; ALOE VERA LEAF; POLYMETHYLSILSESQUIOXANE (4.5 MICRONS); CAPRYLYL GLYCOL; DIMETHICONE; NEOPENTYL GLYCOL DIHEPTANOATE; HYDROGENATED PALM GLYCERIDES; TRISILOXANE; XANTHAN GUM; PHENOXYETHANOL; SODIUM HYDROXIDE; EDETATE DISODIUM ANHYDROUS

WALG SUN MOISTURIZING LOTION SPF50 TUBE

WALGREENS 50 HYDRATING MOISTURIZING BROAD SPECTRUM SUNSCREEN SPF 50 TUBE - Avobenzone, Homosalate, Octisalate, Octocrylene Lotion

WALGREENS 50 HYDRATING MOISTURIZING BROAD SPECTRUM SUNSCREEN SPF 50 TUBE 3 FL OZ (88mL) 41419-400-WG12 (PKTB-41419-WG01)

WALGREENS 50 HYDRATING MOISTURIZING BROAD SPECTRUM SUNSCREEN SPF 50 TUBE 8 FL OZ (236mL) 41420-400-WG12 (PKTB-41420-WG01)

DRUG FACTS

Active Ingredients

Avobenzone 3% (3g/100g)

Homosalate 10% (10g/100g)

Octisalate 4.5% (4.5g/100g)

Octocrylene 8% (8g/100g)

Purpose

Sunscreen

Use

- Helps prevent sunburn
- If used as directed with other sun protection measures (see Directions) decreases the risk of skin cancer and early skin aging caused by the sun

Warnings

- For external use only
- Do not use on damaged or broken skin.
- When using this product keep out of eyes. Rinse with water to remove.
- Stop use and ask a doctor if rash occurs.
- Keep out of reach of children. If swallowed, get medical help or contact a Poison Control Center right away.

Directions

- Apply liberally 15 minutes before sun exposure
- Re-apply:
  • after 80 minutes of swimming or sweating
  • immediately after towel drying
  • at least every 2 hours

Sun Protection Measures. Spending time in the sun increases your risk of skin cancer and early skin aging. To decrease this risk, regularly use a sunscreen with broad spectrum SPF of 15 or higher and other sun protection measures including:

- limit time in the sun, especially from 10 a.m.-2 p.m.
- wear long-sleeved shirts, pants, hats and sunglasses
- Children under 6 months: ask a doctor

Other Information

- Protect the product in this container from excessive heat and direct sun
- May stain fabric

Inactive Ingredients:

Water, Glycerin, Polyglyceryl-3 Methylglucose Distearate, Cetearyl Alcohol, C28-52 Olefin/Undecylenic Acid Copolymer, Tapioca Starch, Acrylates/C12-22 Alkyl Methacrylate Copolymer, Diisopropyl Adipate, Phenethyl Benzoate, Glyceryl Stearate, Potassium Cetyl Phosphate, PEG-100 Stearate, Tocopheryl Acetate, Aloe Barbadensis Leaf Juice, Polymethylsilsesquioxane, Caprylyl Glycol, Dimethicone, Fragrance, Neopentyl Glycol Diheptanoate, Hydrogenated Palm Glycerides, Trisiloxane, Xanthan Gum, Acrylates/C10-30 Alkyl Acrylate Crosspolymer, Phenoxyethanol, Sodium Hydroxide, Disodium EDTA

Questions or comments?

1-800-925-4733

DISTRIBUTED BY: WALGREEN CO.

200 WILMOT RD., DEERFIELD, IL 60015

100% SATISFACTION GUARANTEED

walgreens.com ©2018 Walgreen Co.

41419-400-WG12 (PKTB-041419-WG01) REV-1118 ORG1118-F
41420-400-WG12 (PKTB-41420-WG01) REV-1118 ORG1118-F

Principal Display Panel

Walgreens

50

Hydrating

Broad Spectrum SPF 50

Sunscreen UVA/UVB

HYPOALLERGENIC

OXYBENZONE FREE

PARABEN FREE

Oil free

Water resistant

(80 minutes)

3 FL OZ (88 mL)/8 FL OZ (236 mL)